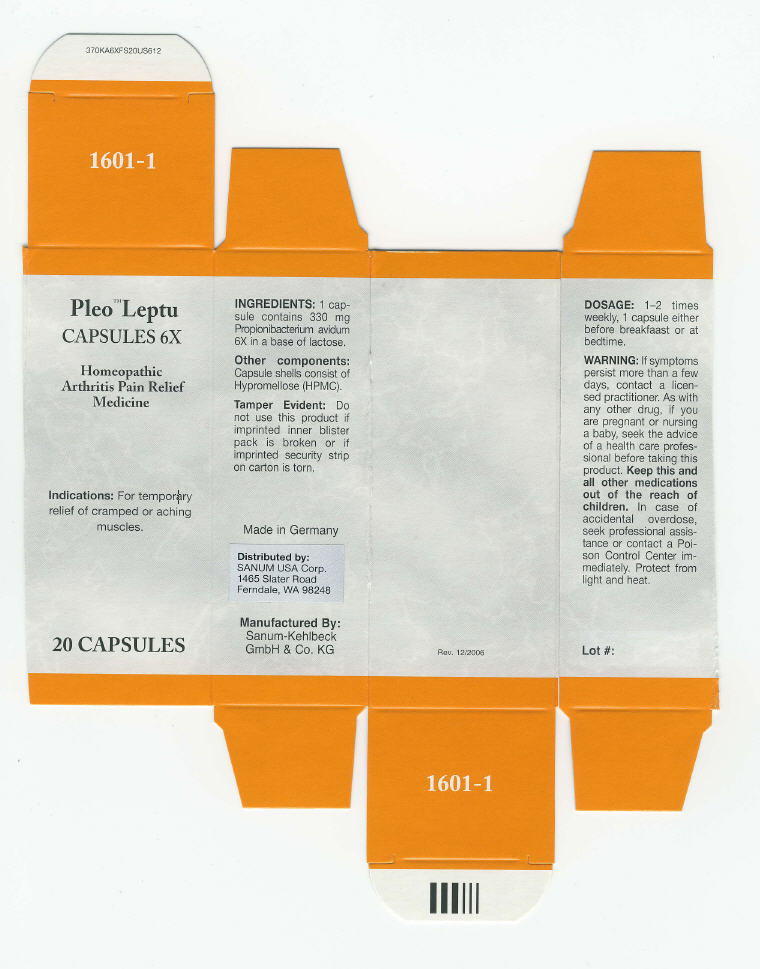 DRUG LABEL: Pleo Leptu
NDC: 60681-1601 | Form: CAPSULE
Manufacturer: Sanum Kehlbeck GmbH & Co. KG
Category: homeopathic | Type: HUMAN OTC DRUG LABEL
Date: 20091009

ACTIVE INGREDIENTS: propionibacterium avidum 6 [HP_X]/1 1
INACTIVE INGREDIENTS: lactose; hypromellose

Pleo™ Leptu
CAPSULES 6X

Homeopathic Arthritis Pain Relief Medicine

20 CAPSULES

Indications

For temporary relief of cramped or aching muscles.

INGREDIENTS

1 capsule contains 330 mg Propionibacterium avidum 6X in a base of lactose.

Other components

Capsule shells consist of Hypromellose (HPMC).

Tamper Evident

Do not use this product if imprinted inner blister pack is broken or if imprinted security strip on carton is torn.

DOSAGE

1–2 times weekly, 1 capsule either before breakfaast or at bedtime.

WARNING

If symptoms persist more than a few days, contact a licensed practitioner. As with any other drug, if you are pregnant or nursing a baby, seek the advice of a health care professional before taking this product.

KEEP OUT OF REACH OF CHILDREN

Keep this and all other medications out of the reach of children. In case of accidental overdose, seek professional assistance or contact a Poison Control Center immediately.

STORAGE AND HANDLING

Protect from light and heat.

Made in Germany

Distributed by:
SANUM USA Corp.
1465 Slater Road
Ferndale, WA 98248

Manufactured By:
Sanum-Kehlbeck
GmbH & Co. KG

Rev. 12/2006

PRINCIPAL DISPLAY PANEL - Capsule Carton

Pleo™ Leptu
CAPSULES 6X

Homeopathic
Arthritis Pain Relief
Medicine

Indications: For temporary
relief of cramped or aching
muscles.

20 CAPSULES